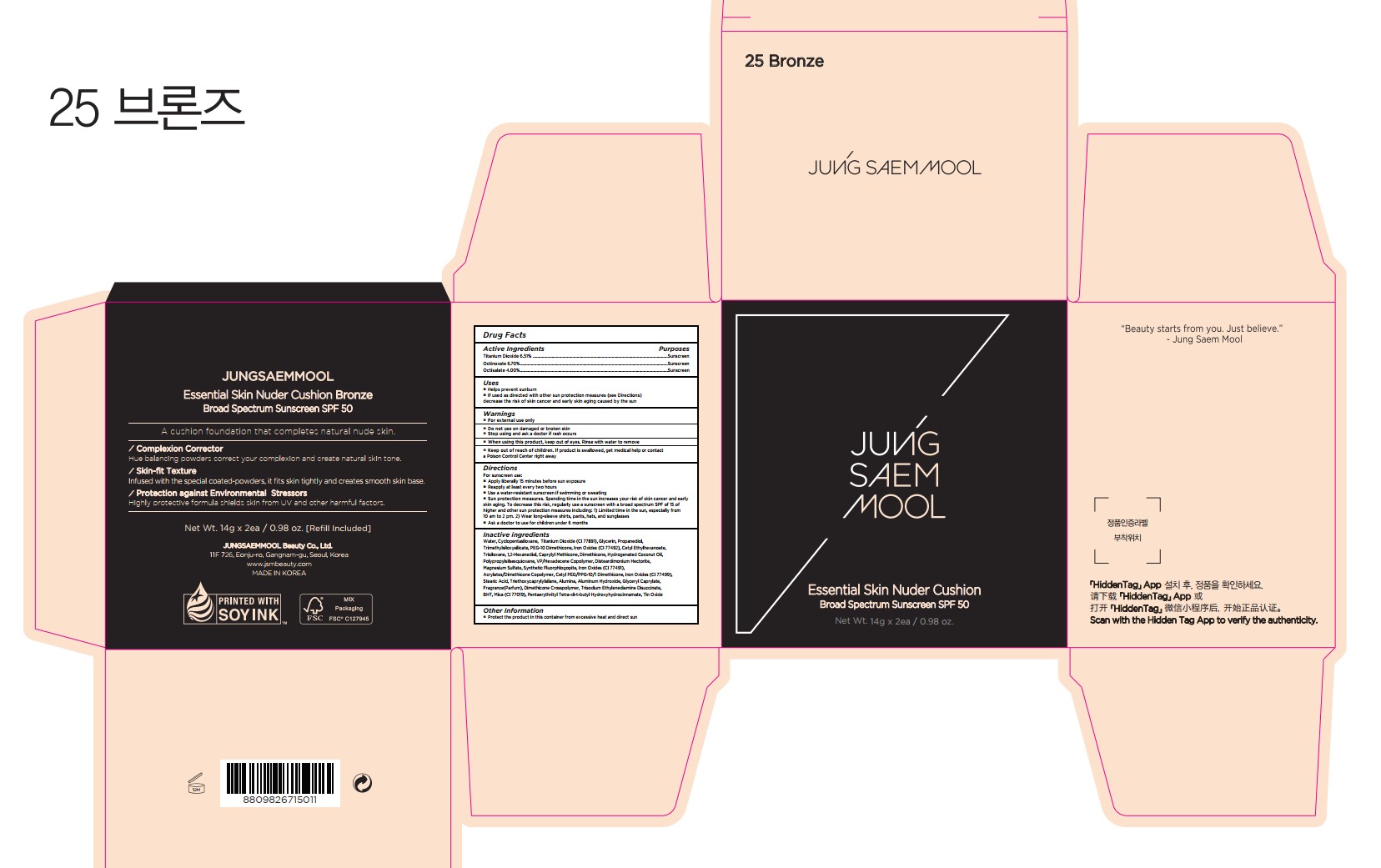 DRUG LABEL: JUNGSAEMMOOL Essential Skin Nuder Cushion Bronze
NDC: 71261-039 | Form: CREAM
Manufacturer: Jungsaemmool Beauty Co., Ltd.
Category: otc | Type: HUMAN OTC DRUG LABEL
Date: 20241014

ACTIVE INGREDIENTS: TITANIUM DIOXIDE 65.1 mg/1 g; OCTINOXATE 67 mg/1 g; OCTISALATE 40 mg/1 g
INACTIVE INGREDIENTS: WATER; CYCLOMETHICONE 5; GLYCERIN; PROPANEDIOL; TRIMETHYLSILOXYSILICATE (M/Q 0.6-0.8); PEG-10 DIMETHICONE (200 CST); FERRIC OXIDE YELLOW; CETYL ETHYLHEXANOATE; TRISILOXANE; 1,2-HEXANEDIOL; CAPRYLYL TRISILOXANE; DIMETHICONE; HYDROGENATED COCONUT OIL; VINYLPYRROLIDONE/HEXADECENE COPOLYMER; DISTEARDIMONIUM HECTORITE; MAGNESIUM SULFATE, UNSPECIFIED FORM; 2-ETHYLHEXYL ACRYLATE, METHACRYLATE, METHYL METHACRYLATE, OR BUTYL METHACRYLATE/HYDROXYPROPYL DIMETHICONE COPOLYMER (30000-300000 MW); FERRIC OXIDE RED; CETYL PEG/PPG-10/1 DIMETHICONE (HLB 4); FERROSOFERRIC OXIDE; STEARIC ACID; TRIETHOXYCAPRYLYLSILANE; ALUMINUM OXIDE; ALUMINUM HYDROXIDE; GLYCERYL MONOCAPRYLATE; DIMETHICONE CROSSPOLYMER; TRISODIUM ETHYLENEDIAMINE DISUCCINATE; BUTYLATED HYDROXYTOLUENE; MICA; PENTAERYTHRITOL TETRAKIS(3-(3,5-DI-TERT-BUTYL-4-HYDROXYPHENYL)PROPIONATE); STANNIC OXIDE

71261-039_JUNGSAEMMOOL Essential Skin Nuder Cushion Bronze

ACTIVE INGREDIENT

Titanium Dioxide 6.51%
Octinoxate 6.70%
Octisalate 4.00%

PURPOSE

Sunscreen

INDICATIONS AND USAGE

Helps prevent sunburn
If used as directed with other sun protection measures (see Directions) decrease the risk of skin cancer and early skin aging caused by the sun

DOSAGE AND ADMINISTRATION

For sunscreen use:
Apply liberally 15 minutes before sun exposure

Reapply at least every two hours
Use a water-resistant sunscreen if swimming or sweating
Sun protection measures. Spending time in the sun increases your risk of skin cancer and early skin aging. To decrease this risk, regularly use a sunscreen with a broad spectrum SPF of 15 of higher and other sun protection measures including: 1) Limited time in the sun, especially from 10 am to 2 pm. 2) Wear long-sleeve shirts, pants, hats, and sunglasses

Ask a doctor to use for children under 6 months

WARNINGS

For external use only

Do not use on damaged or broken skin

When using this product, keep out of eyes. Rinse with water to remove.

Stop using and ask a doctor if rash occurs.

KEEP OUT OF REACH OF CHILDREN

Keep out of reach of the children. If product is swallowed, get medical help or contact a poison control center right away.

INACTIVE INGREDIENT

Water, Cyclopentasiloxane, Titanium Dioxide (CI 77891), Glycerin, Propanediol, Trimethylsiloxysilicate, PEG-10 Dimethicone, Iron Oxides (CI 77492), Cetyl Ethylhexanoate, Trisiloxane, 1,2-Hexanediol, Caprylyl Methicone, Dimethicone, Hydrogenated Coconut Oil, Polypropylsilsesquioxane, VP/Hexadecene Copolymer, Disteardimonium Hectorite, Magnesium Sulfate, Synthetic Fluorphlogopite, Iron Oxides (CI 77491), Acrylates/Dimethicone Copolymer, Cetyl PEG/PPG-10/1 Dimethicone, Iron Oxides (CI 77499), Stearic Acid, Triethoxycaprylylsilane, Alumina, Aluminum Hydroxide, Glyceryl Caprylate, Fragrance(Parfum), Dimethicone Crosspolymer, Trisodium Ethylenediamine Disuccinate, BHT, Mica (CI 77019), Pentaerythrityl Tetra-di-t-butyl Hydroxyhydrocinnamate, Tin Oxide

OTHER SAFETY INFORMATION

Protect the product in the container from excessive heat and direct sun